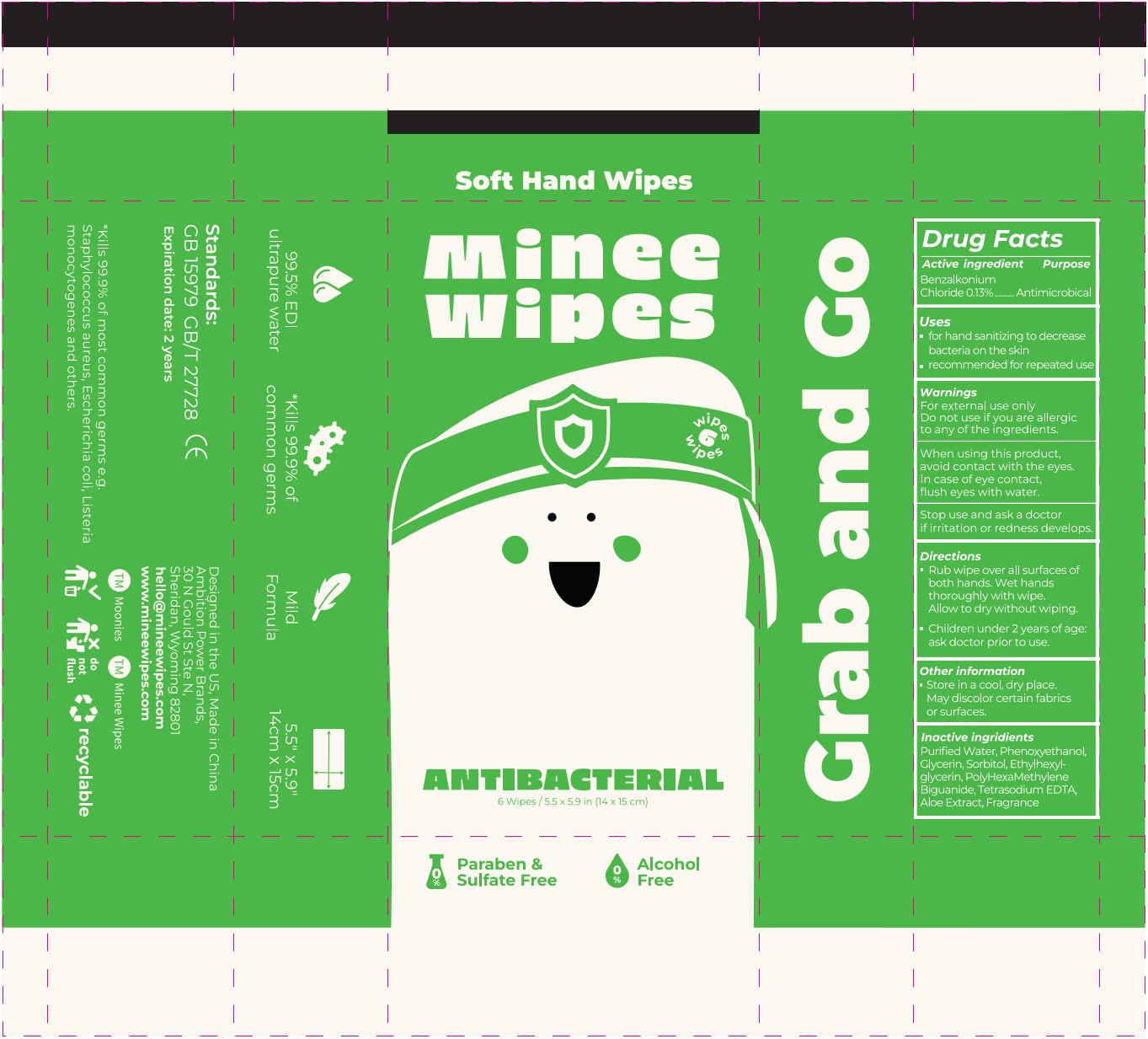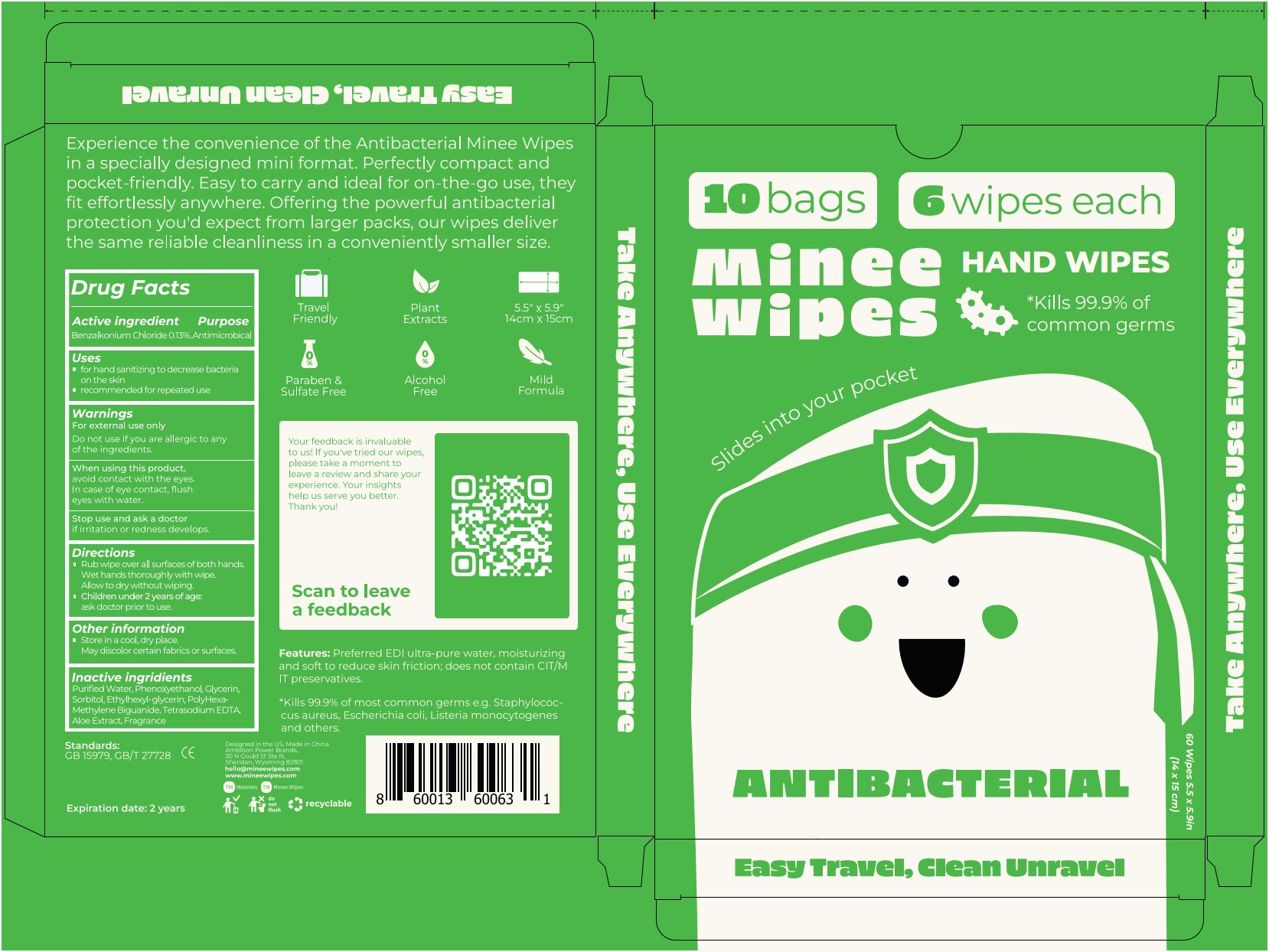 DRUG LABEL: MOONIES Minee Wipes Antibacterial Hand Wipe
NDC: 81361-011 | Form: CLOTH
Manufacturer: Hangzhou Chunchi Touring Commodity Co., Ltd.
Category: otc | Type: HUMAN OTC DRUG LABEL
Date: 20250917

ACTIVE INGREDIENTS: BENZALKONIUM CHLORIDE 13 mg/10000 mg
INACTIVE INGREDIENTS: WATER; PHENOXYETHANOL; GLYCERIN; ETHYLHEXYLGLYCERIN; TETRASODIUM EDTA; GREEN TEA LEAF; POLIHEXANIDE; SORBITOL; ALOE

Wipes, Benzal 0.13%, 6pcs/bag 10bag/box

Active ingredient

Benzalkonium Chloride, 0.13%. Purpose: Antimicrobical

Purpose

Antimicrobical

Uses

- for hand sanitizing to decrease bacteria on the skin
- recommended for repeated use

Warnings

For external use only.

Do not use if you are allergic to any of the ingredients.

Do not use if you are allergic to any of the ingredients.

When using this product,

avoid contact with the eyes.

In case of eye contact, flush eyes with water.

Stop use

if irritation or redness develops.

Ask a doctor

if irritation or redness develops.

Keep out of reach of children.

Directions

- Rub wipe over all surfaces of both hands.

Wet hands throughly with wipe.

Allow to dry without wiping.

- Children under 2 years of age:

ask doctor prior to use.

Other information

- Store in a cool, dry place.

May discolor certain fabrics or surfaces.

Inactive ingredients

Purified Water, Phenoxyethanol, Glycerin, Sorbitol, Ethylhexylglycerin, PolyHexaMethyleneBiguanide, Tetraspdium EDTA, Aloe Extract, Fragrance